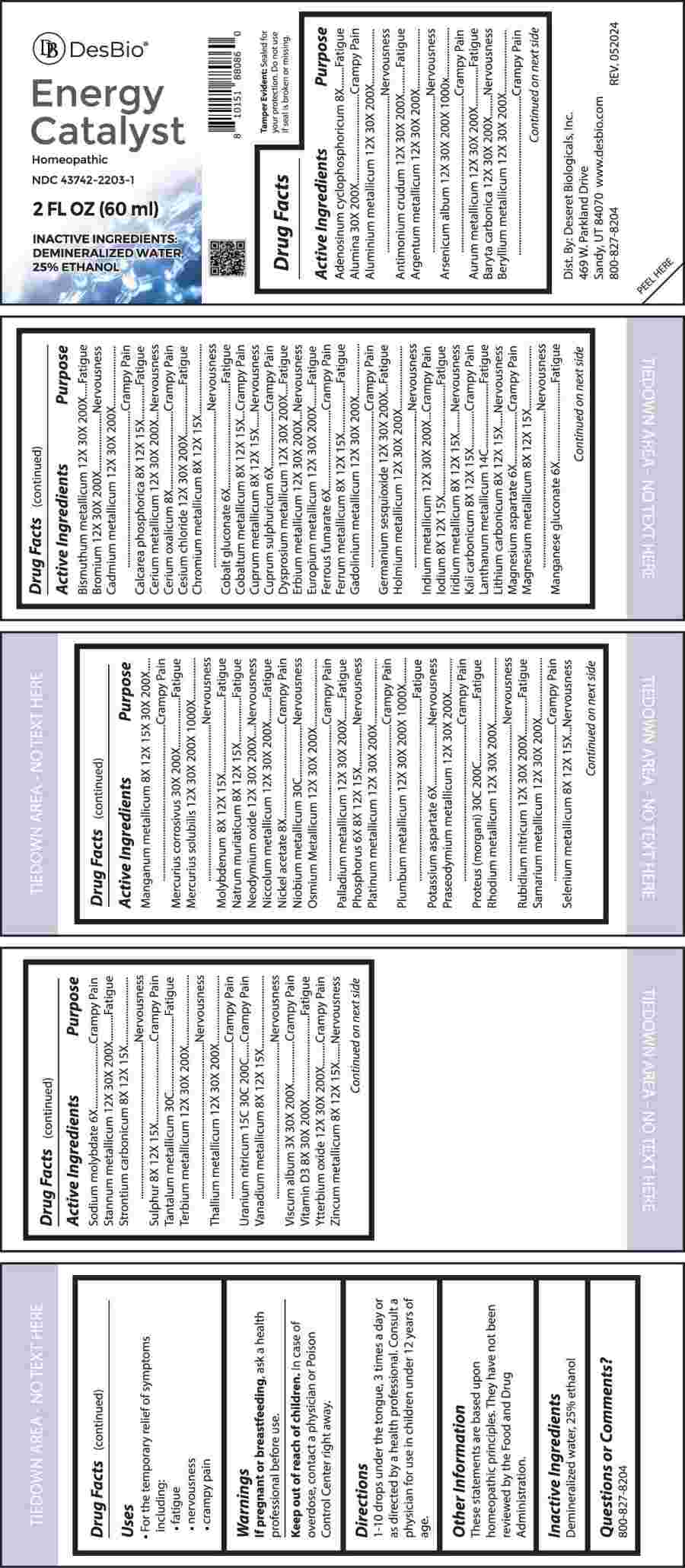 DRUG LABEL: Energy Catalyst
NDC: 43742-2203 | Form: LIQUID
Manufacturer: Deseret Biologicals, Inc.
Category: homeopathic | Type: HUMAN OTC DRUG LABEL
Date: 20241210

ACTIVE INGREDIENTS: ADENOSINE CYCLIC PHOSPHATE 8 [hp_X]/1 mL; ALUMINUM OXIDE 30 [hp_X]/1 mL; ARSENIC TRIOXIDE 12 [hp_X]/1 mL; CEROUS OXALATE NONAHYDRATE 8 [hp_X]/1 mL; COBALTOUS GLUCONATE 6 [hp_X]/1 mL; CUPRIC SULFATE 6 [hp_X]/1 mL; TRIBASIC CALCIUM PHOSPHATE 8 [hp_X]/1 mL; CHROMIUM 8 [hp_X]/1 mL; COBALT 8 [hp_X]/1 mL; COPPER 8 [hp_X]/1 mL; IRON 8 [hp_X]/1 mL; IODINE 8 [hp_X]/1 mL; IRIDIUM 8 [hp_X]/1 mL; POTASSIUM CARBONATE 8 [hp_X]/1 mL; LITHIUM CARBONATE 8 [hp_X]/1 mL; MAGNESIUM 8 [hp_X]/1 mL; MANGANESE 8 [hp_X]/1 mL; MOLYBDENUM 8 [hp_X]/1 mL; SODIUM CHLORIDE 8 [hp_X]/1 mL; PHOSPHORUS 6 [hp_X]/1 mL; SELENIUM 8 [hp_X]/1 mL; STRONTIUM CARBONATE 8 [hp_X]/1 mL; SULFUR 8 [hp_X]/1 mL; VANADIUM 8 [hp_X]/1 mL; ZINC 8 [hp_X]/1 mL; ALUMINUM 12 [hp_X]/1 mL; ANTIMONY TRISULFIDE 12 [hp_X]/1 mL; SILVER 12 [hp_X]/1 mL; GOLD 12 [hp_X]/1 mL; BARIUM CARBONATE 12 [hp_X]/1 mL; BERYLLIUM 12 [hp_X]/1 mL; BISMUTH 12 [hp_X]/1 mL; BROMINE 12 [hp_X]/1 mL; CADMIUM 12 [hp_X]/1 mL; CERIUM 12 [hp_X]/1 mL; CESIUM CHLORIDE 12 [hp_X]/1 mL; DYSPROSIUM 12 [hp_X]/1 mL; ERBIUM 12 [hp_X]/1 mL; EUROPIUM 12 [hp_X]/1 mL; GADOLINIUM 12 [hp_X]/1 mL; GERMANIUM SESQUIOXIDE 12 [hp_X]/1 mL; HOLMIUM 12 [hp_X]/1 mL; INDIUM 12 [hp_X]/1 mL; MERCURIUS SOLUBILIS 12 [hp_X]/1 mL; NEODYMIUM OXIDE 12 [hp_X]/1 mL; NICKEL 12 [hp_X]/1 mL; OSMIUM 12 [hp_X]/1 mL; PALLADIUM 12 [hp_X]/1 mL; PLATINUM 12 [hp_X]/1 mL; LEAD 12 [hp_X]/1 mL; PRASEODYMIUM 12 [hp_X]/1 mL; RHODIUM 12 [hp_X]/1 mL; RUBIDIUM NITRITE 12 [hp_X]/1 mL; SAMARIUM 12 [hp_X]/1 mL; TIN 12 [hp_X]/1 mL; TERBIUM 12 [hp_X]/1 mL; THALLIUM 12 [hp_X]/1 mL; YTTERBIUM OXIDE 12 [hp_X]/1 mL; FERROUS FUMARATE 6 [hp_X]/1 mL; LANTHANUM 14 [hp_C]/1 mL; MAGNESIUM ASPARTATE 6 [hp_X]/1 mL; MANGANESE GLUCONATE 6 [hp_X]/1 mL; MERCURIC CHLORIDE 30 [hp_X]/1 mL; NICKEL ACETATE 8 [hp_X]/1 mL; NIOBIUM 30 [hp_C]/1 mL; POTASSIUM ASPARTATE 6 [hp_X]/1 mL; PROTEUS MORGANII 30 [hp_C]/1 mL; SODIUM MOLYBDATE 6 [hp_X]/1 mL; TANTALUM 30 [hp_C]/1 mL; URANYL NITRATE HEXAHYDRATE 15 [hp_C]/1 mL; VISCUM ALBUM FRUITING TOP 3 [hp_X]/1 mL; CHOLECALCIFEROL 8 [hp_X]/1 mL
INACTIVE INGREDIENTS: WATER; ALCOHOL

DRUG FACTS:

ACTIVE INGREDIENTS:

Adenosinum Cyclophosphoricum 8X, Alumina 30X, 200X, Aluminium Metallicum 12X, 30X, 200X, Antimonium Crudum 12X, 30X, 200X, Argentum Metallicum 12X, 30X, 200X, Arsenicum Album 12X, 30X, 200X, 1000X, Aurum Metallicum 12X, 30X, 200X, Baryta Carbonica 12X, 30X, 200X, Beryllium Metallicum 12X, 30X, 200X, Bismuthum Metallicum 12X, 30X, 200X, Bromium 12X, 30X, 200X, Cadmium Metallicum 12X, 30X, 200X, Calcarea Phosphorica 8X, 12X, 15X, Cerium Metallicum 12X, 30X, 200X, Cerium Oxalicum 8X, Cesium Chloride 12X, 30X, 200X, Chromium Metallicum 8X, 12X, 15X, Cobalt Gluconate 6X, Cobaltum Metallicum 8X, 12X, 15X, Cuprum Metallicum 8X, 12X, 15X, Cuprum Sulphuricum 6X, Dysprosium Metallicum 12X, 30X, 200X, Erbium Metallicum 12X, 30X, 200X, Europium Metallicum 12X, 30X, 200X, Ferrous Fumarate 6X, Ferrum Metallicum 8X, 12X, 15X, Gadolinium Metallicum 12X, 30X, 200X, Germanium Sesquioxide 12X, 30X, 200X, Holmium Metallicum 12X, 30X, 200X, Indium Metallicum 12X, 30X, 200X, Iodium 8X, 12X, 15X, Iridium Metallicum 8X, 12X, 15X, Kali Carbonicum 8X, 12X, 15X, Lanthanum Metallicum 14C, Lithium Carbonicum 8X, 12X, 15X, Magnesium Aspartate 6X, Magnesium Metallicum 8X, 12X, 15X, Manganese Gluconate 6X, Manganum Metallicum 8X, 12X, 15X, 30X, 200X, Mercurius Corrosivus 30X, 200X, Mercurius Solubilis 12X, 30X, 200X, 1000X, Molybdenum 8X, 12X, 15X, Natrum Muriaticum 8X, 12X, 15X, Neodymium Oxide 12X, 30X, 200X, Niccolum Metallicum 12X, 30X, 200X, Nickel Acetate 8X, Niobium Metallicum 30C, Osmium Metallicum 12X, 30X, 200X, Palladium Metallicum 12X, 30X, 200X, Phosphorus 6X, 8X, 12X, 15X, Platinum Metallicum 12X, 30X, 200X, Plumbum Metallicum 12X, 30X, 200X, 1000X, Potassium Aspartate 6X, Praseodymium Metallicum 12X, 30X, 200X, Proteus (Morgani) 30C, 200C, Rhodium Metallicum 12X, 30X, 200X, Rubidium Nitricum 12X, 30X, 200X, Samarium Metallicum 12X, 30X, 200X, Selenium Metallicum 8X, 12X, 15X, Sodium Molybdate 6X, Stannum Metallicum 12X, 30X, 200X, Strontium Carbonicum 8X, 12X, 15X, Sulphur 8X, 12X, 15X, Tantalum Metallicum 30C, Terbium Metallicum 12X, 30X, 200X, Thallium Metallicum 12X, 30X, 200X, Uranium Nitricum 15C, 30C, 200C, Vanadium Metallicum 8X, 12X, 15X, Viscum Album 3X, 30X, 200X, Vitamin D3 8X, 30X, 200X, Ytterbium Oxide 12X, 30X, 200X, Zincum Metallicum 8X, 12X, 15X.

PURPOSE:

Adenosinum Cyclophosphoricum - Fatigue, Alumina – Crampy Pain, Aluminium Metallicum - Nervousness, Antimonium Crudum - Fatigue, Argentum Metallicum - Nervousness, Arsenicum Album – Crampy Pain, Aurum Metallicum - Fatigue, Baryta Carbonica - Nervousness, Beryllium Metallicum – Crampy Pain, Bismuthum Metallicum - Fatigue, Bromium - Nervousness, Cadmium Metallicum – Crampy Pain, Calcarea Phosphorica - Fatigue, Cerium Metallicum - Nervousness, Cerium Oxalicum – Crampy Pain, Cesium Chloride - Fatigue, Chromium Metallicum - Nervousness, Cobalt Gluconate - Fatigue, Cobaltum Metallicum – Crampy Pain, Cuprum Metallicum - Nervousness, Cuprum Sulphuricum – Crampy Pain, Dysprosium Metallicum - Fatigue, Erbium Metallicum - Nervousness, Europium Metallicum - Fatigue, Ferrous Fumarate – Crampy Pain, Ferrum Metallicum - Fatigue, Gadolinium Metallicum – Crampy Pain, Germanium Sesquioxide - Fatigue, Holmium Metallicum - Nervousness, Indium Metallicum – Crampy Pain, Iodium - Fatigue, Iridium Metallicum - Nervousness, Kali Carbonicum – Crampy Pain, Lanthanum Metallicum - Fatigue, Lithium Carbonicum - Nervousness, Magnesium Aspartate - Crampy Pain, Magnesium Metallicum - Nervousness, Manganese Gluconate - Fatigue, Manganum Metallicum – Crampy Pain, Mercurius Corrosivus - Fatigue, Mercurius Solubilis - Nervousness, Molybdenum - Fatigue, Natrum Muriaticum - Fatigue, Neodymium Oxide - Nervousness, Niccolum Metallicum - Fatigue, Nickel Acetate – Crampy Pain, Niobium Metallicum - Nervousness, Osmium Metallicum – Crampy Pain, Palladium Metallicum - Fatigue, Phosphorus - Nervousness, Platinum Metallicum – Crampy Pain, Plumbum Metallicum - Fatigue, Potassium Aspartate - Nervousness, Praseodymium Metallicum – Crampy Pain, Proteus (Morgani) - Fatigue, Rhodium Metallicum - Nervousness, Rubidium Nitricum - Fatigue, Samarium Metallicum – Crampy Pain, Selenium Metallicum - Nervousness, Sodium Molybdate – Crampy Pain, Stannum Metallicum - Fatigue, Strontium Carbonicum - Nervousness, Sulphur – Crampy Pain, Tantalum Metallicum - Fatigue, Terbium Metallicum - Nervousness, Thallium Metallicum – Crampy Pain, Uranium Nitricum – Crampy Pain, Vanadium Metallicum - Nervousness, Viscum Album – Crampy Pain, Vitamin D3 - Fatigue, Ytterbium Oxide – Crampy Pain, Zincum Metallicum - Nervousness

USES:

• For the temporary relief of symptoms including:

• fatigue • nervousness • cramping pains

These statements are based upon homeopathic principles. They have not been reviewed by the Food and Drug Administration.

WARNINGS:

If pregnant or breastfeeding, ask a health professional before use.

Keep out of reach of children. In case of overdose, contact a physician or Poison Control Center right away.

Tamper Evident: Sealed for your protection. Do not use if seal is broken or missing.

KEEP OUT OF REACH OF CHILDREN:

In case of overdose, contact a physician or Poison Control Center right away.

DIRECTIONS:

1-10 drops under the tongue, 3 times a day or as directed by a health professional. Consult a physician for use in children under 12 years of age.

INACTIVE INGREDIENTS:

Demineralized water, 25% Ethanol

QUESTIONS:

Dist. By: Deseret Biologicals, Inc.
469 W. Parkland Drive
Sandy, UT 84070

www.desbio.com

800-827-8204

PACKAGE LABEL DISPLAY:

DesBio

Energy Catalyst

Homeopathic

NDC 43742-2203-1

2 FL OZ (60 ml)